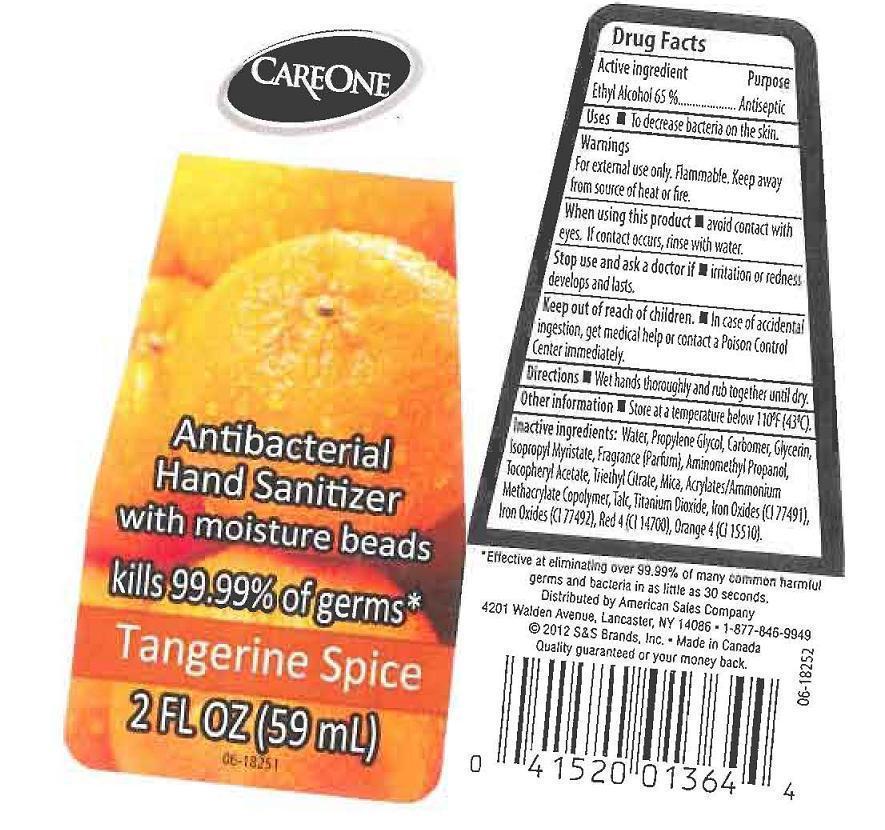 DRUG LABEL: CARE ONE
NDC: 41520-470 | Form: LIQUID
Manufacturer: AMERICAN SALES COMPANY
Category: otc | Type: HUMAN OTC DRUG LABEL
Date: 20120926

ACTIVE INGREDIENTS: ALCOHOL 650 mg/1 mL
INACTIVE INGREDIENTS: WATER; PROPYLENE GLYCOL; CARBOMER 934; GLYCERIN; ISOPROPYL MYRISTATE; AMINOMETHYLPROPANOL; .ALPHA.-TOCOPHEROL ACETATE; TRIETHYL CITRATE; MICA; METHACRYLIC ACID - METHYL METHACRYLATE COPOLYMER (1:1); TALC; TITANIUM DIOXIDE; FERRIC OXIDE RED; FERRIC OXIDE YELLOW; FD&C RED NO. 4; D&C ORANGE NO. 4

DRUG FACTS

ACTIVE INGREDIENT

ETHYL ALCOHOL 65%

PURPOSE

ANTISEPTIC

USES

TO DECREASE BACTERIA ON THE SKIN.

WARNINGS

FOR EXTERNAL USE ONLY. FLAMMABLE. KEEP AWAY FROM SOURCE OF HEAT OR FIRE.

WHEN USING THIS PRODUCT

STOP USE AND ASK A DOCTOR IF

KEEP OUT OF REACH OF CHILDREN

IN CASE OF ACCIDENTAL INGESTION, GET MEDICAL HELP OR CONTACT A POISON CONTROL CENTER IMMEDIATELY.

DIRECTIONS

WET ANDS THOROUGHLY AND RUB TOGETHER UNTIL DRY.

OTHER INFORMATION

STORE AT A TEMPERATURE BELOW 110F (43C).

INACTIVE INGREDIENTS:

WATER (AQUA), pROPYLENE GLYCOL, CARBOMER, GLYCERIN, ISOPROPYL MYRISTATE, FRAGRANCE (PARFUM), AMINOMETHYL PROPANOL, TOCOPHERYL ACETATE, TRIETHYL CITRATE, MICA, ACRYLATES/AMMONIUM METHACRYLATE COPOLYMER, TALC, TITANIUM DIOXIDE, IRON OXIDES (CI 77491), IRON OXIDES (CI 77492), RED 4 (CI 14700), ORANGE 4 (CI 15510).